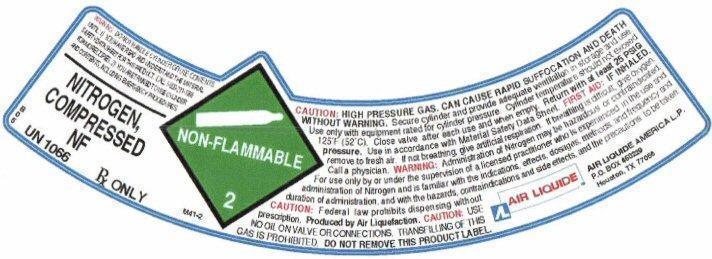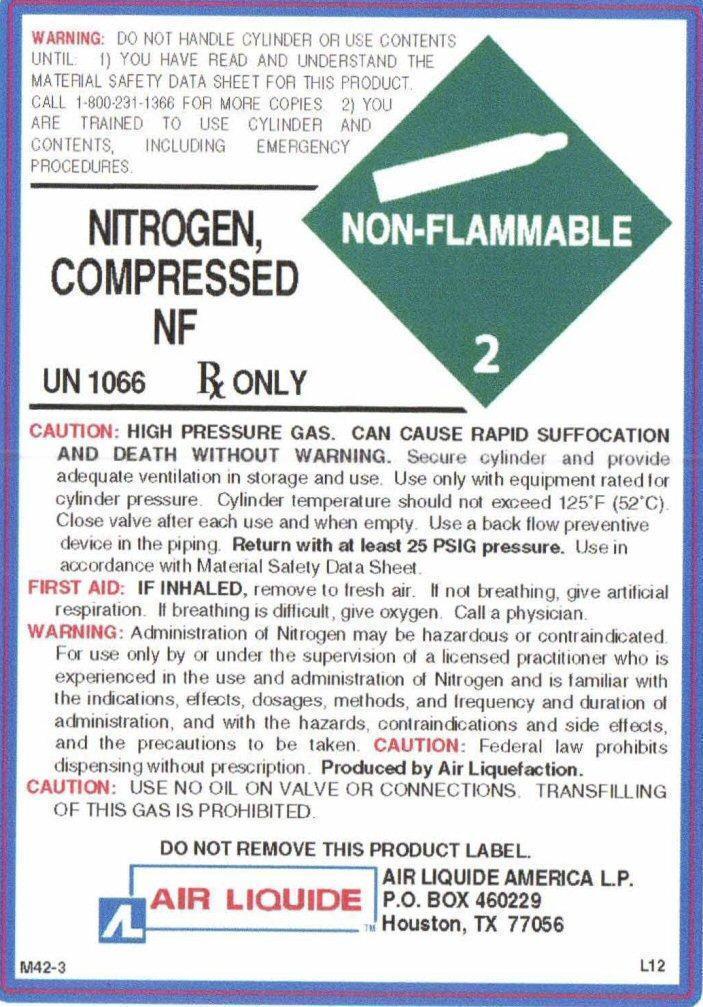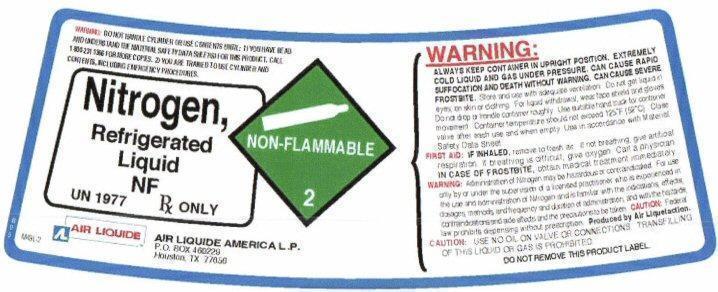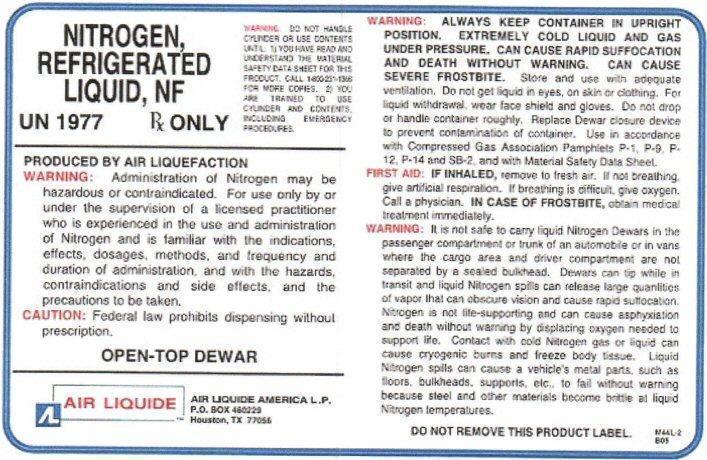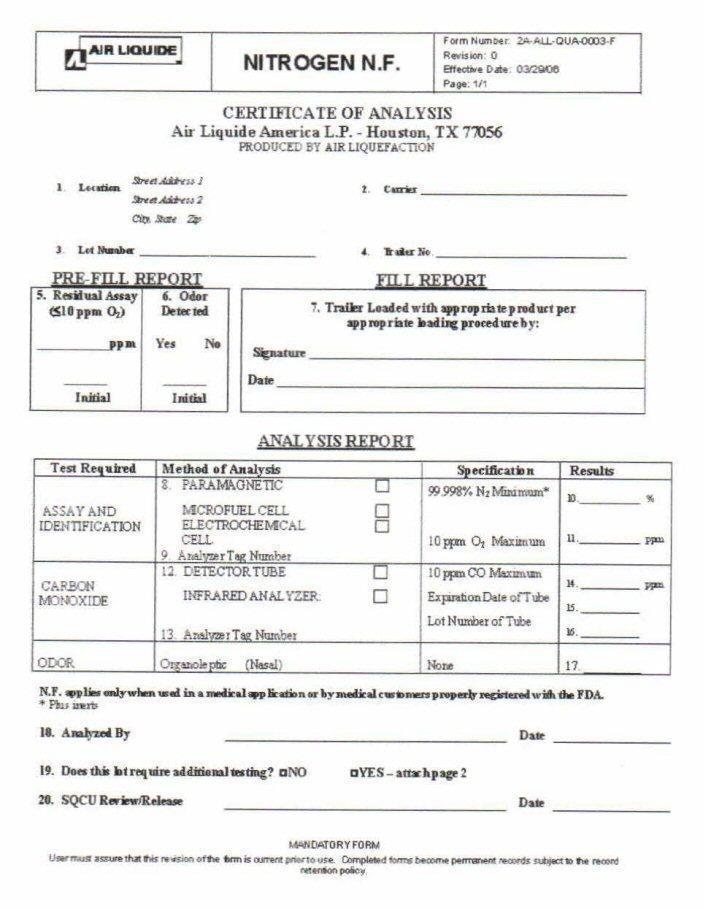 DRUG LABEL: NITROGEN
NDC: 10671-020 | Form: GAS
Manufacturer: Air Liquide America L.P.
Category: prescription | Type: HUMAN PRESCRIPTION DRUG LABEL
Date: 20150219

ACTIVE INGREDIENTS: NITROGEN 99 L/100 L

NITROGEN COMPRESSED NF SL

WARNING: DO NOT HANDLE CYLINDER OR USE CONTENTS UNTIL: 1) YOU HAVE READ AND UNDERSTAND THE MATERIAL SAFETY DATA SHEET FOR THIS PRODUCT. CALL 1-800-231-1366 FOR MORE COPIES. 2) YOU ARE TRAINED TO USE CYLINDER AND CONTENTS, INCLUDING EMERGENCY PROCEDURES.

NITROGEN COMPRESSED NF
NON-FLAMMABLE 2

BO5 UN 1066 Rx ONLY M41-2

CAUTION: HIGH PRESSURE GAS. CAN CAUSE RAPID SUFFOCATION AND DEATH WITHOUT WARNING.

Secure cylinder and provide adequate ventilation in storage and use. Use only with equipment rated for cylinder pressure. Cylinder temperature should not exceed 125° F (52° C). Close valve after each use and when empty.

Return with at least 25 PSIG pressure.

Use in accordance with the Material Safety Data Sheet.

FIRST AID: IF INHALED, remove to fresh air. If not breathing, give artificial respiration. If breathing is difficult, give oxygen. Call a physician.

WARNING: Administration of Nitrogen may be hazardous or contraindicated. For use only by or under the supervision of a licensed practitioner who is experienced in the use and administration of Nitrogen and is familiar with the indications, effects, dosages, methods, and frequency and duration of administration, and with the hazards, contraindications, and side effects and the precautions to be taken.

CAUTION: Federal law prohibits dispensing without prescription.

Produced by Air Liquefaction.

CAUTION: USE NO OIL ON VALVE OR CONNECTIONS. TRANSFILLING OF THIS GAS IS PROHIBITED.

DO NOT REMOVE THIS PRODUCT LABEL

AIR LIQUIDE AMERICA L.P.
P.O.BOX 460229
Houston, TX 77056

NTROGEN COMPRESSED NF LABEL

WARNING: DO NOT HANDLE CYLINDER OR USE CONTENTS UNTIL: 1) YOU HAVE READ AND UNDERSTAND THE MATERIAL SAFETY DATA SHEET FOR THIS PRODUCT. CALL 1-800-231-1366 FOR MORE COPIES. 2) YOU ARE TRAINED TO USE CYLINDER AND CONTENTS, INCLUDING EMERGENCY PROCEDURES.
NITROGEN COMPRESSED NF
NON-FLAMMABLE 2
BO5 UN 1066 Rx ONLY M41-2
CAUTION: HIGH PRESSURE GAS. CAN CAUSE RAPID SUFFOCATION AND DEATH WITHOUT WARNING.
Secure cylinder and provide adequate ventilation in storage and use. Use only with equipment rated for cylinder pressure. Cylinder temperature should not exceed 125° F (52° C). Close valve after each use and when empty. Use a back flow preventive device in the piping.
Return with at least 25 PSIG pressure.
Use in accordance with the Material Safety Data Sheet.
FIRST AID: IF INHALED, remove to fresh air. If not breathing, give artificial respiration. If breathing is difficult, give oxygen. Call a
physician.
WARNING: Administration of Nitrogen may be hazardous or contraindicated. For use only by or under the supervision of a licensed practitioner who is experienced in the use and administration of Nitrogen and is familiar with the indications, effects, dosages, methods, and frequency and duration of administration, and with the hazards, contraindications, and side effects and the precautions to be taken.
CAUTION: Federal law prohibits dispensing without prescription.
Produced by Air Liquefaction.
CAUTION: USE NO OIL ON VALVE OR CONNECTIONS. TRANSFILLING OF THIS GAS IS PROHIBITED.
DO NOT REMOVE THIS PRODUCT LABEL
AIR LIQUIDE AMERICA L.P.
P.O.BOX 460229
Houston, TX 77056

M42-3 L12

NITROGEN REFRIGERATED LIQUID NF Label

WARNING: DO NOT HANDLE CYLINDER OR USE CONTENTS UNTIL: 1) YOU HAVE READ AND UNDERSTAND THE MATERIAL SAFETY DATA SHEET FOR THIS PRODUCT. CALL 1-800-231-1366 FOR MORE COPIES. 2) YOU ARE TRAINED TO USE CYLINDER AND CONTENTS, INCLUDING EMERGENCY PROCEDURES.

Nitrogen, Refrigerated Liquid NF

NON-FLAMMABLE 2

UN 1977 Rx ONLY M43L-2

AIR LIQUIDE
P.O. Box 4602229
Houston, Tx 77056

WARNING: ALWAYS KEEP CONTAINER IN UPRIGHT POSITION. EXTREMELY COLD LIQUID AND GAS UNDER PRESSURE. CAN CAUSE RAPID SUFFOCATION AND DEATH WITHOUT WARNING. CAN CAUSE SEVERE FROSTBITE.
Store and use with adequate ventilation. Do not get liquid in eyes, on skin or clothing. For liquid withdrawal, wear face shield and gloves. Do not drop or handle container roughly. Use suitable hand truck for container movement. Container temperature should not exceed 125°F (52°C). Close valve after each use and when empty. Use in accordance with Material Safety Data Sheet.
FIRST AID: IF INHALED, remove to fresh air. If not breathing, give artificial respiration. If breathing is difficult, give oxygen. Call a physician.

IN CASE OF FROSTBITE, obtain medical treatment immediately.
WARNING: Administration of Nitrogen may be hazardous or contraindicated. For use only by or under the supervision of a licensed practitioner who is experienced in the use and administration of Nitrogen and is familiar with the indications, effects, dosages, methods, and frequency and duration of administration, and with the hazards, contraindications and side effects, and the precautions to be taken.
CAUTION: Federal law prohibits dispensing without prescription.

Produced by Air Liquefaction.
CAUTION: USE NO OIL ON VALVE OR CONNECTIONS. TRANSFILLING OF THIS LIQUID OR GAS IS PROHIBITED.
DO NOT REMOVE THIS PRODUCT LABEL.

NITROGEN, REFRIGERATED LIQUID, NF Label

WARNING: DO NOT HANDLE CYLINDER OR USE CONTENTS UNTIL: 1) YOU HAVE READ AND UNDERSTAND THE MATERIAL SAFETY DATA SHEET FOR THIS PRODUCT. CALL 1-800-231-1366 FOR MORE COPIES. 2) YOU ARE TRAINED TO USE CYLINDER AND CONTENTS, INCLUDING EMERGENCY PROCEDURES.

NITROGEN REFRIGERATED LIQUID, NF

UN 1977 Rx ONLY

PRODUCED BY AIR LIQUEFACTION.
WARNING: Administration of Nitrogen may be hazardous or contraindicated. For use only by or under the supervision of a licensed practitioner who is experienced in the use and administration of Nitrogen and is familiar with the indications, effects, dosages, methods, and frequency and duration of administration, and with the hazards, contraindications and side effects, and the precautions to be taken.
CAUTION: Federal law prohibits dispensing without prescription.

OPEN-TOP DEWAR

AIR LIQUIDE AMERICA L.P.
P.O. BOX 460229
Houston, TX 77056
WARNING: ALWAYS KEEP CONTAINER IN UPRIGHT POSITION. EXTREMELY COLD LIQUID AND GAS UNDER PRESSURE. CAN CAUSE RAPID SUFFOCATION AND DEATH WITHOUT WARNING. CAN CAUSE SEVERE FROSTBITE.
Store and use with adequate ventilation. Do not get liquid in eyes, on skin or clothing. For liquid withdrawal, wear face shield and gloves. Do not drop or handle container roughly. Replace Dewar closure device to prevent contamination of container. Use in accordance with Compressed Gas Association Pamphlets P-1, P-9, P-12, P-14 and SB-2, and with Material Safety Data Sheet.
FIRST AID: IF INHALED, remove to fresh air. If not breathing, give artificial respiration. If breathing is difficult, give oxygen. Call a physician.

IN CASE OF FROSTBITE, obtain medical treatment immediately.
WARNING: It is not safe to carry liquid Nitrogen Dewars in the passenger compartment or trunk of an automobile or in vans where the cargo area and driver compartment are not separated by a sealed bulkhead. Dewars can tip while in transit and liquid Nitrogen spills can release large quantities of vapor that can obscure vision and cause rapid suffocation. Nitrogen is not life-supporting and can cause asphyxiation and death without warning by displacing oxygen needed to support life. Contact with cold Nitrogen gas or liquid can cause cryogenic burns and freeze body tissue. Liquid Nitrogen spills can cause a vehicle's metal parts, such as floors, bulkheads, supports, etc., to fail without warning because steel and other materials become brittle at liquid Nitrogen temperatures.
DO NOT REMOVE THIS PRODUCT LABEL. M44L-2 B05

NITROGEN COA

NITROGEN N.F. CERTIFICATE OF ANALYSIS